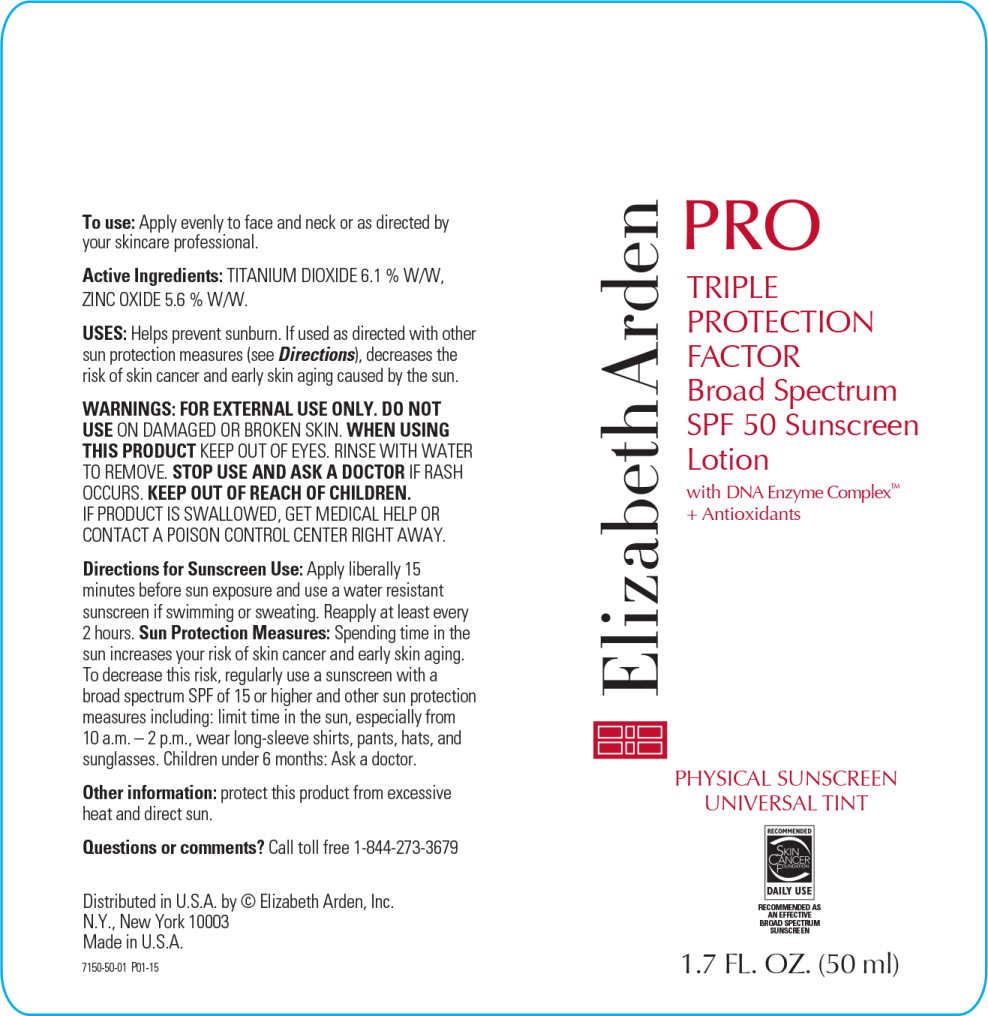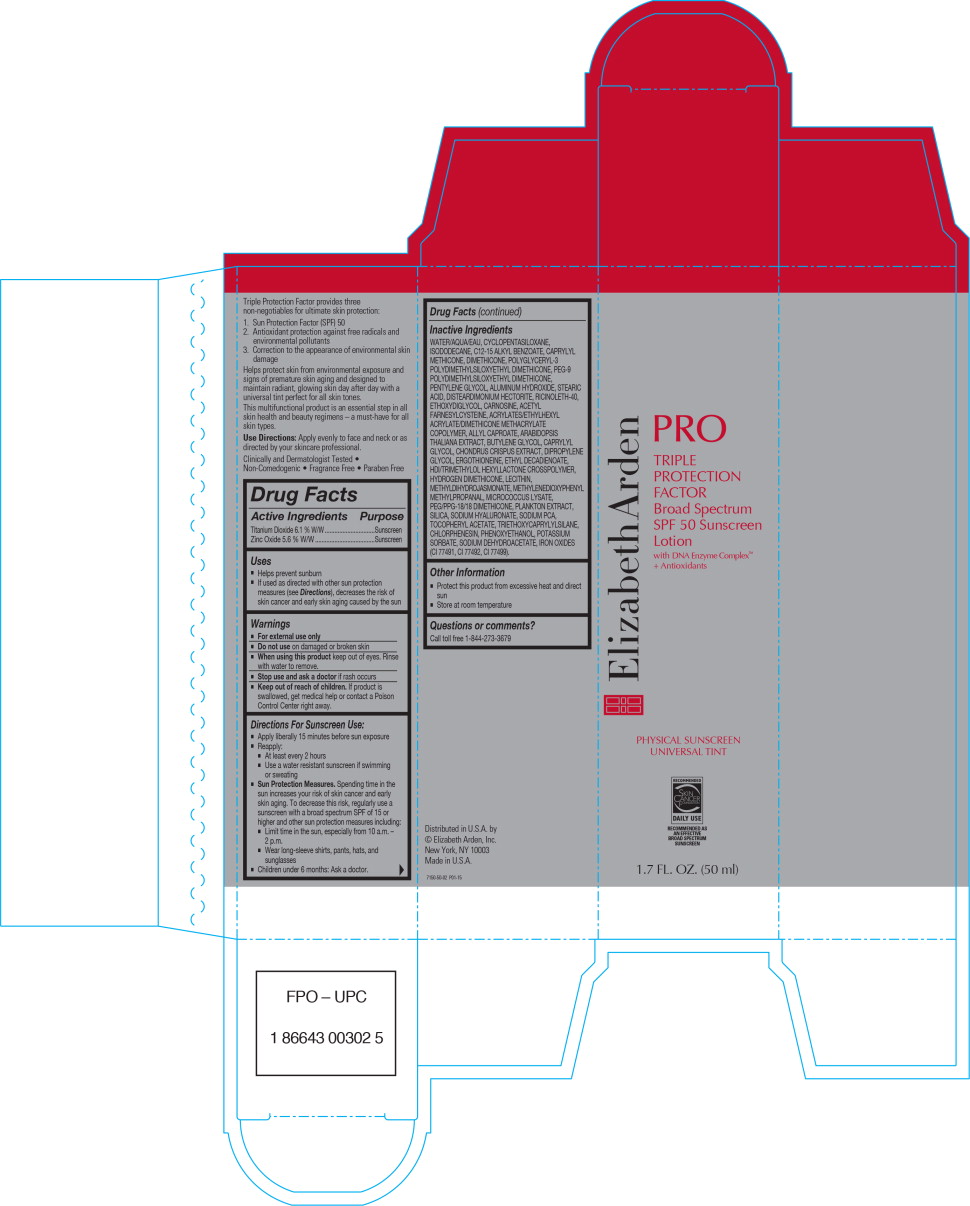 DRUG LABEL: PRO TRIPLE PROTECTION FACTOR BROAD SPECTRUM SPF 50 SUNSCREEN
NDC: 67938-2075 | Form: LOTION
Manufacturer: ELIZABETH ARDEN, INC
Category: otc | Type: HUMAN OTC DRUG LABEL
Date: 20170201

ACTIVE INGREDIENTS: TITANIUM DIOXIDE .25803 g/1 mL; ZINC OXIDE .31416 g/1 mL
INACTIVE INGREDIENTS: WATER; CYCLOMETHICONE 5; ISODODECANE; ALKYL (C12-15) BENZOATE; CAPRYLYL TRISILOXANE; DIMETHICONE; POLYGLYCERYL-3 POLYDIMETHYLSILOXYETHYL DIMETHICONE (4000 MPA.S); PEG-9 POLYDIMETHYLSILOXYETHYL DIMETHICONE; PENTYLENE GLYCOL; STEARIC ACID; ALUMINUM HYDROXIDE; RICINOLETH-40; CARNOSINE; DIETHYLENE GLYCOL MONOETHYL ETHER; DISTEARDIMONIUM HECTORITE; HEXAMETHYLENE DIISOCYANATE/TRIMETHYLOL HEXYLLACTONE CROSSPOLYMER; PHENOXYETHANOL; SODIUM PYRROLIDONE CARBOXYLATE; ACETYL FARNESYLCYSTEINE; FERRIC OXIDE YELLOW; CAPRYLYL GLYCOL; PEG/PPG-18/18 DIMETHICONE; CHLORPHENESIN; FERRIC OXIDE RED; METHYL DIHYDROJASMONATE (SYNTHETIC); ALLYL HEXANOATE; ETHYL 2,4-DECADIENOATE, (2E,4Z)-; DIPROPYLENE GLYCOL; 3-(3,4-METHYLENEDIOXYPHENYL)-2-METHYLPROPANAL; CHONDRUS CRISPUS CARRAGEENAN; FERROSOFERRIC OXIDE; SILICON DIOXIDE; TRIETHOXYCAPRYLYLSILANE; LECITHIN, SOYBEAN; POTASSIUM SORBATE; .ALPHA.-TOCOPHEROL ACETATE; BUTYLENE GLYCOL; ARABIDOPSIS THALIANA; SODIUM DEHYDROACETATE; ERGOTHIONEINE; HYALURONATE SODIUM

Drug Facts

Active Ingredients

Titanium Dioxide 6.1 % W/W

Zinc Oxide 5.6 % W/W

Purpose

Sunscreen

Sunscreen

Uses

- Helps prevent sunburn
- If used as directed with other sun protection measures (see Directions), decreases the risk of skin cancer and early skin aging caused by the sun

Warnings

- For external use only

- Do not use on damaged or broken skin

- When using this product keep out of eyes. Rinse with water to remove.

- Stop use and ask a doctor if rash occurs

- Keep out of reach of children. If product is swallowed, get medical help or contact a Poison Control Center right away.

Directions For Sunscreen Use:

- Apply liberally 15 minutes before sun exposure
- Reapply:
  - At least every 2 hours
  - Use a water resistant sunscreen if swimming or sweating
- Sun Protection Measures. Spending time in the sun increases your risk of skin cancer and early skin aging. To decrease this risk, regularly use a sunscreen with a broad spectrum SPF of 15 or higher and other sun protection measures including:
  - Limit time in the sun, especially from 10 a.m. – 2 p.m.
  - Wear long-sleeve shirts, pants, hats, and sunglasses
- Children under 6 months: Ask a doctor.

Inactive Ingredients

WATER/AQUA/EAU, CYCLOPENTASILOXANE, ISODODECANE, C12-15 ALKYL BENZOATE, CAPRYLYL METHICONE, DIMETHICONE, POLYGLYCERYL-3 POLYDIMETHYLSILOXYETHYL DIMETHICONE, PEG-9 POLYDIMETHYLSILOXYETHYL DIMETHICONE, PENTYLENE GLYCOL, ALUMINUM HYDROXIDE, STEARIC ACID, DISTEARDIMONIUM HECTORITE, RICINOLETH-40, ETHOXYDIGLYCOL, CARNOSINE, ACETYL FARNESYLCYSTEINE, ACRYLATES/ETHYLHEXYL ACRYLATE/DIMETHICONE METHACRYLATE COPOLYMER, ALLYL CAPROATE, ARABIDOPSIS THALIANA EXTRACT, BUTYLENE GLYCOL, CAPRYLYL GLYCOL, CHONDRUS CRISPUS EXTRACT, DIPROPYLENE GLYCOL, ERGOTHIONEINE, ETHYL DECADIENOATE, HDI/TRIMETHYLOL HEXYLLACTONE CROSSPOLYMER, HYDROGEN DIMETHICONE, LECITHIN, METHYLDIHYDROJASMONATE, METHYLENEDIOXYPHENYL METHYLPROPANAL, MICROCOCCUS LYSATE, PEG/PPG-18/18 DIMETHICONE, PLANKTON EXTRACT, SILICA, SODIUM HYALURONATE, SODIUM PCA, TOCOPHERYL ACETATE, TRIETHOXYCAPRYLYLSILANE, CHLORPHENESIN, PHENOXYETHANOL, POTASSIUM SORBATE, SODIUM DEHYDROACETATE, IRON OXIDES (CI 77491, CI 77492, CI 77499).

Other Information

- Protect this product from excessive heat and direct sun
- Store at room temperature

Questions or comments?

Call toll free 1-844-273-3679

Principal Display Panel - Bottle Label

ElizabethArden

PRO

TRIPLE
PROTECTION
FACTOR

Broad Spectrum
SPF 50 Sunscreen
Lotion

with DNA Enzyme Complex™
+ Antioxidants

PHYSICAL SUNSCREEN
UNIVERSAL TINT

RECOMMENDED

SKIN
CANCER
FOUNDATION

DAILY USE

RECOMMENDED AS
AN EFFECTIVE
BROAD SPECTRUM
SUNSCREEN

1.7 FL. OZ. (50 ml)

Principal Display Panel - Carton Label

ElizabethArden

PRO

TRIPLE
PROTECTION
FACTOR

Broad Spectrum
SPF 50 Sunscreen
Lotion

with DNA Enzyme Complex™
+ Antioxidants

PHYSICAL SUNSCREEN
UNIVERSAL TINT

RECOMMENDED

SKIN
CANCER
FOUNDATION

DAILY USE

RECOMMENDED AS
AN EFFECTIVE
BROAD SPECTRUM
SUNSCREEN

1.7 FL. OZ. (50 ml)